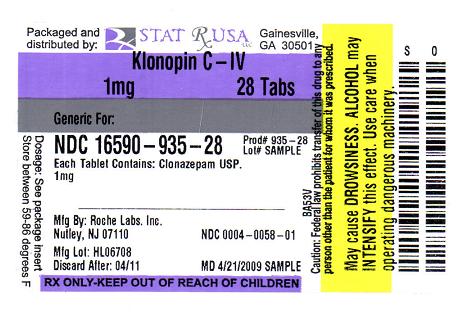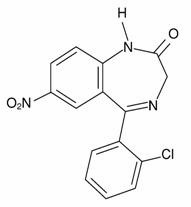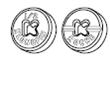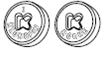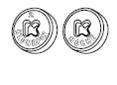 DRUG LABEL: KLONOPIN
NDC: 16590-935 | Form: TABLET
Manufacturer: STAT RX USA LLC
Category: prescription | Type: HUMAN PRESCRIPTION DRUG LABEL
Date: 20110322
DEA Schedule: CIV

ACTIVE INGREDIENTS: CLONAZEPAM 1 mg/1 1
INACTIVE INGREDIENTS: LACTOSE; MAGNESIUM STEARATE; CELLULOSE, MICROCRYSTALLINE; STARCH, CORN; FD&C BLUE NO. 1; ALUMINUM OXIDE; FD&C BLUE NO. 2

CIV

DESCRIPTION

Klonopin, a benzodiazepine, is available as scored tablets with a K-shaped perforation containing 0.5 mg of clonazepam and unscored tablets with a K-shaped perforation containing 1 mg or 2 mg of clonazepam. Each tablet also contains lactose, magnesium stearate, microcrystalline cellulose and corn starch, with the following colorants: 0.5 mg—FD&C Yellow No. 6 Lake; 1 mg—FD&C Blue No. 1 Lake and FD&C Blue No. 2 Lake.

Klonopin is also available as an orally disintegrating tablet containing 0.125 mg, 0.25 mg, 0.5 mg, 1 mg or 2 mg clonazepam. Each orally disintegrating tablet also contains gelatin, mannitol, methylparaben sodium, propylparaben sodium and xanthan gum.

Chemically, clonazepam is 5-(2-chlorophenyl)-1,3-dihydro-7-nitro-2H-1,4-benzodiazepin-2-one. It is a light yellow crystalline powder. It has a molecular weight of 315.72 and the following structural formula:

CLINICAL PHARMACOLOGY

Pharmacodynamics

The precise mechanism by which clonazepam exerts its antiseizure and antipanic effects is unknown, although it is believed to be related to its ability to enhance the activity of gamma aminobutyric acid (GABA), the major inhibitory neurotransmitter in the central nervous system. Convulsions produced in rodents by pentylenetetrazol or, to a lesser extent, electrical stimulation are antagonized, as are convulsions produced by photic stimulation in susceptible baboons. A taming effect in aggressive primates, muscle weakness and hypnosis are also produced. In humans, clonazepam is capable of suppressing the spike and wave discharge in absence seizures (petit mal) and decreasing the frequency, amplitude, duration and spread of discharge in minor motor seizures.

Pharmacokinetics

Clonazepam is rapidly and completely absorbed after oral administration. The absolute bioavailability of clonazepam is about 90%. Maximum plasma concentrations of clonazepam are reached within 1 to 4 hours after oral administration. Clonazepam is approximately 85% bound to plasma proteins. Clonazepam is highly metabolized, with less than 2% unchanged clonazepam being excreted in the urine. Biotransformation occurs mainly by reduction of the 7-nitro group to the 4-amino derivative. This derivative can be acetylated, hydroxylated and glucuronidated. Cytochrome P-450 including CYP3A, may play an important role in clonazepam reduction and oxidation. The elimination half-life of clonazepam is typically 30 to 40 hours. Clonazepam pharmacokinetics are dose-independent throughout the dosing range. There is no evidence that clonazepam induces its own metabolism or that of other drugs in humans.

Pharmacokinetics in Demographic Subpopulations and in Disease States

Controlled studies examining the influence of gender and age on clonazepam pharmacokinetics have not been conducted, nor have the effects of renal or liver disease on clonazepam pharmacokinetics been studied. Because clonazepam undergoes hepatic metabolism, it is possible that liver disease will impair clonazepam elimination. Thus, caution should be exercised when administering clonazepam to these patients.

Clinical Trials

Panic Disorder

The effectiveness of Klonopin in the treatment of panic disorder was demonstrated in two double-blind, placebo-controlled studies of adult outpatients who had a primary diagnosis of panic disorder (DSM-IIIR) with or without agoraphobia. In these studies, Klonopin was shown to be significantly more effective than placebo in treating panic disorder on change from baseline in panic attack frequency, the Clinician's Global Impression Severity of Illness Score and the Clinician's Global Impression Improvement Score.

Study 1 was a 9-week, fixed-dose study involving Klonopin doses of 0.5, 1, 2, 3 or 4 mg/day or placebo. This study was conducted in four phases: a 1-week placebo lead-in, a 3-week upward titration, a 6-week fixed dose and a 7-week discontinuance phase. A significant difference from placebo was observed consistently only for the 1 mg/day group. The difference between the 1 mg dose group and placebo in reduction from baseline in the number of full panic attacks was approximately 1 panic attack per week. At endpoint, 74% of patients receiving clonazepam 1 mg/day were free of full panic attacks, compared to 56% of placebo-treated patients.

Study 2 was a 6-week, flexible-dose study involving Klonopin in a dose range of 0.5 to 4 mg/day or placebo. This study was conducted in three phases: a 1-week placebo lead-in, a 6-week optimal-dose and a 6-week discontinuance phase. The mean clonazepam dose during the optimal dosing period was 2.3 mg/day. The difference between Klonopin and placebo in reduction from baseline in the number of full panic attacks was approximately 1 panic attack per week. At endpoint, 62% of patients receiving clonazepam were free of full panic attacks, compared to 37% of placebo-treated patients.

Subgroup analyses did not indicate that there were any differences in treatment outcomes as a function of race or gender.

INDICATIONS AND USAGE

Seizure Disorders

Klonopin is useful alone or as an adjunct in the treatment of the Lennox-Gastaut syndrome (petit mal variant), akinetic and myoclonic seizures. In patients with absence seizures (petit mal) who have failed to respond to succinimides, Klonopin may be useful.

In some studies, up to 30% of patients have shown a loss of anticonvulsant activity, often within 3 months of administration. In some cases, dosage adjustment may reestablish efficacy.

Panic Disorder

Klonopin is indicated for the treatment of panic disorder, with or without agoraphobia, as defined in DSM-IV. Panic disorder is characterized by the occurrence of unexpected panic attacks and associated concern about having additional attacks, worry about the implications or consequences of the attacks, and/or a significant change in behavior related to the attacks.

The efficacy of Klonopin was established in two 6- to 9-week trials in panic disorder patients whose diagnoses corresponded to the DSM-IIIR category of panic disorder (see CLINICAL PHARMACOLOGY: Clinical Trials).

Panic disorder (DSM-IV) is characterized by recurrent unexpected panic attacks, ie, a discrete period of intense fear or discomfort in which four (or more) of the following symptoms develop abruptly and reach a peak within 10 minutes: (1) palpitations, pounding heart or accelerated heart rate; (2) sweating; (3) trembling or shaking; (4) sensations of shortness of breath or smothering; (5) feeling of choking; (6) chest pain or discomfort; (7) nausea or abdominal distress; (8) feeling dizzy, unsteady, lightheaded or faint; (9) derealization (feelings of unreality) or depersonalization (being detached from oneself); (10) fear of losing control; (11) fear of dying; (12) paresthesias (numbness or tingling sensations); (13) chills or hot flushes.

The effectiveness of Klonopin in long-term use, that is, for more than 9 weeks, has not been systematically studied in controlled clinical trials. The physician who elects to use Klonopin for extended periods should periodically reevaluate the long-term usefulness of the drug for the individual patient (see DOSAGE AND ADMINISTRATION).

CONTRAINDICATIONS

Klonopin should not be used in patients with a history of sensitivity to benzodiazepines, nor in patients with clinical or biochemical evidence of significant liver disease. It may be used in patients with open angle glaucoma who are receiving appropriate therapy but is contraindicated in acute narrow angle glaucoma.

WARNINGS

Interference With Cognitive and Motor Performance

Since Klonopin produces CNS depression, patients receiving this drug should be cautioned against engaging in hazardous occupations requiring mental alertness, such as operating machinery or driving a motor vehicle. They should also be warned about the concomitant use of alcohol or other CNS-depressant drugs during Klonopin therapy (see PRECAUTIONS: Drug Interactions and Information for Patients).

Suicidal Behavior and Ideation

Antiepileptic drugs (AEDs), including Klonopin, increase the risk of suicidal thoughts or behavior in patients taking these drugs for any indication. Patients treated with any AED for any indication should be monitored for the emergence or worsening of depression, suicidal thoughts or behavior, and/or any unusual changes in mood or behavior.

Pooled analyses of 199 placebo-controlled clinical trials (mono- and adjunctive therapy) of 11 different AEDs showed that patients randomized to one of the AEDs had approximately twice the risk (adjusted Relative Risk 1.8, 95% CI:1.2, 2.7) of suicidal thinking or behavior compared to patients randomized to placebo. In these trials, which had a median treatment duration of 12 weeks, the estimated incidence rate of suicidal behavior or ideation among 27,863 AED-treated patients was 0.43% compared to 0.24% among 16,029 placebo-treated patients, representing an increase of approximately one case of suicidal thinking or behavior for every 530 patients treated. There were four suicides in drug-treated patients in the trials and none in placebo-treated patients, but the number is too small to allow any conclusion about drug effect on suicide.

The increased risk of suicidal thoughts or behavior with AEDs was observed as early as one week after starting drug treatment with AEDs and persisted for the duration of treatment assessed. Because most trials included in the analysis did not extend beyond 24 weeks, the risk of suicidal thoughts or behavior beyond 24 weeks could not be assessed.

The risk of suicidal thoughts or behavior was generally consistent among drugs in the data analyzed. The finding of increased risk with AEDs of varying mechanisms of action and across a range of indications suggests that the risk applies to all AEDs used for any indication. The risk did not vary substantially by age (5-100 years) in the clinical trials analyzed.

Table 1 shows absolute and relative risk by indication for all evaluated AEDs.

Table 1 Risk by Indication for Antiepileptic Drugs in the Pooled Analysis
Indication | Placebo Patients with Events Per 1000 Patients | Drug Patients with Events Per 1000 Patients | Relative Risk: Incidence of Events in Drug Patients/Incidence in Placebo Patients | Risk Difference: Additional Drug Patients with Events per 1000 Patients
Epilepsy | 1.0 | 3.4 | 3.5 | 2.4
Psychiatric | 5.7 | 8.5 | 1.5 | 2.9
Other | 1.0 | 1.8 | 1.9 | 0.9
Total | 2.4 | 4.3 | 1.8 | 1.9

The relative risk for suicidal thoughts or behavior was higher in clinical trials for epilepsy than in clinical trials for psychiatric or other conditions, but the absolute risk differences were similar for the epilepsy and psychiatric indications.

Anyone considering prescribing Klonopin or any other AED must balance the risk of suicidal thoughts or behavior with the risk of untreated illness. Epilepsy and many other illnesses for which AEDs are prescribed are themselves associated with morbidity and mortality and an increased risk of suicidal thoughts and behavior. Should suicidal thoughts and behavior emerge during treatment, the prescriber needs to consider whether the emergence of these symptoms in any given patient may be related to the illness being treated.

Patients, their caregivers, and families should be informed that AEDs increase the risk of suicidal thoughts and behavior and should be advised of the need to be alert for the emergence or worsening of the signs and symptoms of depression, any unusual changes in mood or behavior, or the emergence of suicidal thoughts, behavior, or thoughts about self-harm. Behaviors of concern should be reported immediately to healthcare providers.

Pregnancy Risks

Data from several sources raise concerns about the use of Klonopin during pregnancy.

Animal Findings

In three studies in which Klonopin was administered orally to pregnant rabbits at doses of 0.2, 1, 5 or 10 mg/kg/day (low dose approximately 0.2 times the maximum recommended human dose of 20 mg/day for seizure disorders and equivalent to the maximum dose of 4 mg/day for panic disorder, on a mg/m^2 basis) during the period of organogenesis, a similar pattern of malformations (cleft palate, open eyelid, fused sternebrae and limb defects) was observed in a low, non-dose-related incidence in exposed litters from all dosage groups. Reductions in maternal weight gain occurred at dosages of 5 mg/kg/day or greater and reduction in embryo-fetal growth occurred in one study at a dosage of 10 mg/kg/day. No adverse maternal or embryo-fetal effects were observed in mice and rats following administration during organogenesis of oral doses up to 15 mg/kg/day or 40 mg/kg/day, respectively (4 and 20 times the maximum recommended human dose of 20 mg/day for seizure disorders and 20 and 100 times the maximum dose of 4 mg/day for panic disorder, respectively, on a mg/m^2 basis).

General Concerns and Considerations About Anticonvulsants

Recent reports suggest an association between the use of anticonvulsant drugs by women with epilepsy and an elevated incidence of birth defects in children born to these women. Data are more extensive with respect to diphenylhydantoin and phenobarbital, but these are also the most commonly prescribed anticonvulsants; less systematic or anecdotal reports suggest a possible similar association with the use of all known anticonvulsant drugs.

In children of women treated with drugs for epilepsy, reports suggesting an elevated incidence of birth defects cannot be regarded as adequate to prove a definite cause and effect relationship. There are intrinsic methodologic problems in obtaining adequate data on drug teratogenicity in humans; the possibility also exists that other factors (eg, genetic factors or the epileptic condition itself) may be more important than drug therapy in leading to birth defects. The great majority of mothers on anticonvulsant medication deliver normal infants. It is important to note that anticonvulsant drugs should not be discontinued in patients in whom the drug is administered to prevent seizures because of the strong possibility of precipitating status epilepticus with attendant hypoxia and threat to life. In individual cases where the severity and frequency of the seizure disorder are such that the removal of medication does not pose a serious threat to the patient, discontinuation of the drug may be considered prior to and during pregnancy; however, it cannot be said with any confidence that even mild seizures do not pose some hazards to the developing embryo or fetus.

General Concerns About Benzodiazepines

An increased risk of congenital malformations associated with the use of benzodiazepine drugs has been suggested in several studies.

There may also be non-teratogenic risks associated with the use of benzodiazepines during pregnancy. There have been reports of neonatal flaccidity, respiratory and feeding difficulties, and hypothermia in children born to mothers who have been receiving benzodiazepines late in pregnancy. In addition, children born to mothers receiving benzodiazepines late in pregnancy may be at some risk of experiencing withdrawal symptoms during the postnatal period.

Advice Regarding the Use of Klonopin in Women of Childbearing Potential

In general, the use of Klonopin in women of childbearing potential, and more specifically during known pregnancy, should be considered only when the clinical situation warrants the risk to the fetus.

The specific considerations addressed above regarding the use of anticonvulsants for epilepsy in women of childbearing potential should be weighed in treating or counseling these women.

Because of experience with other members of the benzodiazepine class, Klonopin is assumed to be capable of causing an increased risk of congenital abnormalities when administered to a pregnant woman during the first trimester. Because use of these drugs is rarely a matter of urgency in the treatment of panic disorder, their use during the first trimester should almost always be avoided. The possibility that a woman of childbearing potential may be pregnant at the time of institution of therapy should be considered. If this drug is used during pregnancy, or if the patient becomes pregnant while taking this drug, the patient should be apprised of the potential hazard to the fetus. Patients should also be advised that if they become pregnant during therapy or intend to become pregnant, they should communicate with their physician about the desirability of discontinuing the drug.

Withdrawal Symptoms

Withdrawal symptoms of the barbiturate type have occurred after the discontinuation of benzodiazepines (see DRUG ABUSE AND DEPENDENCE).

PRECAUTIONS

General

Worsening of Seizures

When used in patients in whom several different types of seizure disorders coexist, Klonopin may increase the incidence or precipitate the onset of generalized tonic-clonic seizures (grand mal). This may require the addition of appropriate anticonvulsants or an increase in their dosages. The concomitant use of valproic acid and Klonopin may produce absence status.

Laboratory Testing During Long-Term Therapy

Periodic blood counts and liver function tests are advisable during long-term therapy with Klonopin.

Risks of Abrupt Withdrawal

The abrupt withdrawal of Klonopin, particularly in those patients on long-term, high-dose therapy, may precipitate status epilepticus. Therefore, when discontinuing Klonopin, gradual withdrawal is essential. While Klonopin is being gradually withdrawn, the simultaneous substitution of another anticonvulsant may be indicated.

Caution in Renally Impaired Patients

Metabolites of Klonopin are excreted by the kidneys; to avoid their excess accumulation, caution should be exercised in the administration of the drug to patients with impaired renal function.

Hypersalivation

Klonopin may produce an increase in salivation. This should be considered before giving the drug to patients who have difficulty handling secretions. Because of this and the possibility of respiratory depression, Klonopin should be used with caution in patients with chronic respiratory diseases.

Information for Patients

A Klonopin Medication Guide must be given to the patient each time Klonopin is dispensed, as required by law. Patients should be instructed to take Klonopin only as prescribed. Physicians are advised to discuss the following issues with patients for whom they prescribe Klonopin:

Dose Changes

To assure the safe and effective use of benzodiazepines, patients should be informed that, since benzodiazepines may produce psychological and physical dependence, it is advisable that they consult with their physician before either increasing the dose or abruptly discontinuing this drug.

Interference With Cognitive and Motor Performance

Because benzodiazepines have the potential to impair judgment, thinking or motor skills, patients should be cautioned about operating hazardous machinery, including automobiles, until they are reasonably certain that Klonopin therapy does not affect them adversely.

Suicidal Thinking and Behavior

Patients, their caregivers, and families should be counseled that AEDs, including Klonopin, may increase the risk of suicidal thoughts and behavior and should be advised of the need to be alert for the emergence or worsening of symptoms of depression, any unusual changes in mood or behavior, or the emergence of suicidal thoughts, behavior, or thoughts about self-harm. Behaviors of concern should be reported immediately to healthcare providers.

Pregnancy

Patients should be advised to notify their physician if they become pregnant or intend to become pregnant during therapy with Klonopin (see WARNINGS: Pregnancy Risks). Patients should be encouraged to enroll in the North American Antiepileptic Drug (NAAED) Pregnancy Registry if they become pregnant. This registry is collecting information about the safety of antiepileptic drugs during pregnancy. To enroll, patients can call the toll free number 1-888-233-2334 (see PRECAUTIONS: Pregnancy).

Nursing

Patients should be advised not to breastfeed an infant if they are taking Klonopin.

Concomitant Medication

Patients should be advised to inform their physicians if they are taking, or plan to take, any prescription or over-the-counter drugs, since there is a potential for interactions.

Alcohol

Patients should be advised to avoid alcohol while taking Klonopin.

Drug Interactions

Effect of Clonazepam on the Pharmacokinetics of Other Drugs

Clonazepam does not appear to alter the pharmacokinetics of phenytoin, carbamazepine or phenobarbital. The effect of clonazepam on the metabolism of other drugs has not been investigated.

Effect of Other Drugs on the Pharmacokinetics of Clonazepam

Literature reports suggest that ranitidine, an agent that decreases stomach acidity, does not greatly alter clonazepam pharmacokinetics.

In a study in which the 2 mg clonazepam orally disintegrating tablet was administered with and without propantheline (an anticholinergic agent with multiple effects on the GI tract) to healthy volunteers, the AUC of clonazepam was 10% lower and the Cmax of clonazepam was 20% lower when the orally disintegrating tablet was given with propantheline compared to when it was given alone.

Fluoxetine does not affect the pharmacokinetics of clonazepam. Cytochrome P-450 inducers, such as phenytoin, carbamazepine and phenobarbital, induce clonazepam metabolism, causing an approximately 30% decrease in plasma clonazepam levels. Although clinical studies have not been performed, based on the involvement of the cytochrome P-450 3A family in clonazepam metabolism, inhibitors of this enzyme system, notably oral antifungal agents, should be used cautiously in patients receiving clonazepam.

Pharmacodynamic Interactions

The CNS-depressant action of the benzodiazepine class of drugs may be potentiated by alcohol, narcotics, barbiturates, nonbarbiturate hypnotics, antianxiety agents, the phenothiazines, thioxanthene and butyrophenone classes of antipsychotic agents, monoamine oxidase inhibitors and the tricyclic antidepressants, and by other anticonvulsant drugs.

Carcinogenesis, Mutagenesis, Impairment of Fertility

Carcinogenicity studies have not been conducted with clonazepam.

The data currently available are not sufficient to determine the genotoxic potential of clonazepam.

In a two-generation fertility study in which clonazepam was given orally to rats at 10 and 100 mg/kg/day (low dose approximately 5 times and 24 times the maximum recommended human dose of 20 mg/day for seizure disorder and 4 mg/day for panic disorder, respectively, on a mg/m^2 basis), there was a decrease in the number of pregnancies and in the number of offspring surviving until weaning.

Pregnancy

Teratogenic Effects

Pregnancy Category D

(see WARNINGS: Pregnancy Risks).

To provide information regarding the effects of in utero exposure to Klonopin, physicians are advised to recommend that pregnant patients taking Klonopin enroll in the NAAED Pregnancy Registry. This can be done by calling the toll free number 1-888-233-2334, and must be done by patients themselves. Information on this registry can also be found at the website http://www.aedpregnancyregistry.org/.

Labor and Delivery

The effect of Klonopin on labor and delivery in humans has not been specifically studied; however, perinatal complications have been reported in children born to mothers who have been receiving benzodiazepines late in pregnancy, including findings suggestive of either excess benzodiazepine exposure or of withdrawal phenomena (see WARNINGS: Pregnancy Risks).

Nursing Mothers

Mothers receiving Klonopin should not breastfeed their infants.

Pediatric Use

Because of the possibility that adverse effects on physical or mental development could become apparent only after many years, a benefit-risk consideration of the long-term use of Klonopin is important in pediatric patients being treated for seizure disorder (see INDICATIONS AND USAGE and DOSAGE AND ADMINISTRATION).

Safety and effectiveness in pediatric patients with panic disorder below the age of 18 have not been established.

Geriatric Use

Clinical studies of Klonopin did not include sufficient numbers of subjects aged 65 and over to determine whether they respond differently from younger subjects. Other reported clinical experience has not identified differences in responses between the elderly and younger patients. In general, dose selection for an elderly patient should be cautious, usually starting at the low end of the dosing range, reflecting the greater frequency of decreased hepatic, renal, or cardiac function, and of concomitant disease or other drug therapy.

Because clonazepam undergoes hepatic metabolism, it is possible that liver disease will impair clonazepam elimination. Metabolites of Klonopin are excreted by the kidneys; to avoid their excess accumulation, caution should be exercised in the administration of the drug to patients with impaired renal function. Because elderly patients are more likely to have decreased hepatic and/or renal function, care should be taken in dose selection, and it may be useful to assess hepatic and/or renal function at the time of dose selection.

Sedating drugs may cause confusion and over-sedation in the elderly; elderly patients generally should be started on low doses of Klonopin and observed closely.

ADVERSE REACTIONS

The adverse experiences for Klonopin are provided separately for patients with seizure disorders and with panic disorder.

Seizure Disorders

The most frequently occurring side effects of Klonopin are referable to CNS depression. Experience in treatment of seizures has shown that drowsiness has occurred in approximately 50% of patients and ataxia in approximately 30%. In some cases, these may diminish with time; behavior problems have been noted in approximately 25% of patients. Others, listed by system, are:

Neurologic: Abnormal eye movements, aphonia, choreiform movements, coma, diplopia, dysarthria, dysdiadochokinesis, ''glassy-eyed'' appearance, headache, hemiparesis, hypotonia, nystagmus, respiratory depression, slurred speech, tremor, vertigo

Psychiatric: Confusion, depression, amnesia, hallucinations, hysteria, increased libido, insomnia, psychosis (the behavior effects are more likely to occur in patients with a history of psychiatric disturbances). The following paradoxical reactions have been observed: excitability, irritability, aggressive behavior, agitation, nervousness, hostility, anxiety, sleep disturbances, nightmares and vivid dreams

Respiratory: Chest congestion, rhinorrhea, shortness of breath, hypersecretion in upper respiratory passages

Cardiovascular: Palpitations

Dermatologic: Hair loss, hirsutism, skin rash, ankle and facial edema

Gastrointestinal: Anorexia, coated tongue, constipation, diarrhea, dry mouth, encopresis, gastritis, increased appetite, nausea, sore gums

Genitourinary: Dysuria, enuresis, nocturia, urinary retention

Musculoskeletal: Muscle weakness, pains

Miscellaneous: Dehydration, general deterioration, fever, lymphadenopathy, weight loss or gain

Hematopoietic: Anemia, leukopenia, thrombocytopenia, eosinophilia

Hepatic: Hepatomegaly, transient elevations of serum transaminases and alkaline phosphatase

Panic Disorder

Adverse events during exposure to Klonopin were obtained by spontaneous report and recorded by clinical investigators using terminology of their own choosing. Consequently, it is not possible to provide a meaningful estimate of the proportion of individuals experiencing adverse events without first grouping similar types of events into a smaller number of standardized event categories. In the tables and tabulations that follow, CIGY dictionary terminology has been used to classify reported adverse events, except in certain cases in which redundant terms were collapsed into more meaningful terms, as noted below.

The stated frequencies of adverse events represent the proportion of individuals who experienced, at least once, a treatment-emergent adverse event of the type listed. An event was considered treatment-emergent if it occurred for the first time or worsened while receiving therapy following baseline evaluation.

Adverse Findings Observed in Short-Term, Placebo-Controlled Trials

Adverse Events Associated With Discontinuation of Treatment

Overall, the incidence of discontinuation due to adverse events was 17% in Klonopin compared to 9% for placebo in the combined data of two 6- to 9-week trials. The most common events (≥1%) associated with discontinuation and a dropout rate twice or greater for Klonopin than that of placebo included the following:

Table 2 Most Common Adverse Events (≥1%) Associated with Discontinuation of Treatment
Adverse Event | Klonopin (N=574) | Placebo (N=294)
Somnolence | 7% | 1%
Depression | 4% | 1%
Dizziness | 1% | <1%
Nervousness | 1% | 0%
Ataxia | 1% | 0%
Intellectual Ability Reduced | 1% | 0%

Adverse Events Occurring at an Incidence of 1% or More Among Klonopin-Treated Patients

Table 3 enumerates the incidence, rounded to the nearest percent, of treatment-emergent adverse events that occurred during acute therapy of panic disorder from a pool of two 6- to 9-week trials. Events reported in 1% or more of patients treated with Klonopin (doses ranging from 0.5 to 4 mg/day) and for which the incidence was greater than that in placebo-treated patients are included.

The prescriber should be aware that the figures in Table 3 cannot be used to predict the incidence of side effects in the course of usual medical practice where patient characteristics and other factors differ from those that prevailed in the clinical trials. Similarly, the cited frequencies cannot be compared with figures obtained from other clinical investigations involving different treatments, uses and investigators. The cited figures, however, do provide the prescribing physician with some basis for estimating the relative contribution of drug and nondrug factors to the side effect incidence in the population studied.

Table 3 Treatment-Emergent Adverse Event Incidence in 6- to 9-Week Placebo-Controlled Clinical Trials [Events reported by at least 1% of patients treated with Klonopin and for which the incidence was greater than that for placebo.]
Clonazepam Maximum Daily Dose
Adverse Event by Body System | <1mg n=96 % | 1-<2mg n=129 % | 2-<3mg n=113 % | ≥3mg n=235 % | All Klonopin Groups N=574 % | Placebo N=294 %
Central & Peripheral Nervous System
Somnolence [Indicates that the p-value for the dose-trend test (Cochran-Mantel-Haenszel) for adverse event incidence was ≤0.10.] | 26 | 35 | 50 | 36 | 37 | 10
Dizziness | 5 | 5 | 12 | 8 | 8 | 4
Coordination Abnormal | 1 | 2 | 7 | 9 | 6 | 0
Ataxia | 2 | 1 | 8 | 8 | 5 | 0
Dysarthria | 0 | 0 | 4 | 3 | 2 | 0
Psychiatric
Depression | 7 | 6 | 8 | 8 | 7 | 1
Memory Disturbance | 2 | 5 | 2 | 5 | 4 | 2
Nervousness | 1 | 4 | 3 | 4 | 3 | 2
Intellectual Ability Reduced | 0 | 2 | 4 | 3 | 2 | 0
Emotional Lability | 0 | 1 | 2 | 2 | 1 | 1
Libido Decreased | 0 | 1 | 3 | 1 | 1 | 0
Confusion | 0 | 2 | 2 | 1 | 1 | 0
Respiratory System
Upper Respiratory Tract Infection | 10 | 10 | 7 | 6 | 8 | 4
Sinusitis | 4 | 2 | 8 | 4 | 4 | 3
Rhinitis | 3 | 2 | 4 | 2 | 2 | 1
Coughing | 2 | 2 | 4 | 0 | 2 | 0
Pharyngitis | 1 | 1 | 3 | 2 | 2 | 1
Bronchitis | 1 | 0 | 2 | 2 | 1 | 1
Gastrointestinal System
Constipation | 0 | 1 | 5 | 3 | 2 | 2
Appetite Decreased | 1 | 1 | 0 | 3 | 1 | 1
Abdominal Pain | 2 | 2 | 2 | 0 | 1 | 1
Body as a Whole
Fatigue | 9 | 6 | 7 | 7 | 7 | 4
Allergic Reaction | 3 | 1 | 4 | 2 | 2 | 1
Musculoskeletal
Myalgia | 2 | 1 | 4 | 0 | 1 | 1
Resistance Mechanism Disorders
Influenza | 3 | 2 | 5 | 5 | 4 | 3
Urinary System
Micturition Frequency | 1 | 2 | 2 | 1 | 1 | 0
Urinary Tract Infection | 0 | 0 | 2 | 2 | 1 | 0
Vision Disorders
Blurred Vision | 1 | 2 | 3 | 0 | 1 | 1
Reproductive Disorders [Denominators for events in gender-specific systems are: n=240 (clonazepam), 102 (placebo) for male, and 334 (clonazepam), 192 (placebo) for female.]
Female
Dysmenorrhea | 0 | 6 | 5 | 2 | 3 | 2
Colpitis | 4 | 0 | 2 | 1 | 1 | 1
Male
Ejaculation Delayed | 0 | 0 | 2 | 2 | 1 | 0
Impotence | 3 | 0 | 2 | 1 | 1 | 0

Commonly Observed Adverse Events

Table 4 Incidence of Most Commonly Observed Adverse Events [Treatment-emergent events for which the incidence in the clonazepam patients was ≥5% and at least twice that in the placebo patients.] in Acute Therapy in Pool of 6- to 9-Week Trials
Adverse Event (Genentech Preferred Term) | Clonazepam (N=574) | Placebo (N=294)
Somnolence | 37% | 10%
Depression | 7% | 1%
Coordination Abnormal | 6% | 0%
Ataxia | 5% | 0%

Treatment-Emergent Depressive Symptoms

In the pool of two short-term placebo-controlled trials, adverse events classified under the preferred term "depression" were reported in 7% of Klonopin-treated patients compared to 1% of placebo-treated patients, without any clear pattern of dose relatedness. In these same trials, adverse events classified under the preferred term "depression" were reported as leading to discontinuation in 4% of Klonopin-treated patients compared to 1% of placebo-treated patients. While these findings are noteworthy, Hamilton Depression Rating Scale (HAM-D) data collected in these trials revealed a larger decline in HAM-D scores in the clonazepam group than the placebo group suggesting that clonazepam-treated patients were not experiencing a worsening or emergence of clinical depression.

Other Adverse Events Observed During the Premarketing Evaluation of Klonopin in Panic Disorder

Following is a list of modified CIGY terms that reflect treatment-emergent adverse events reported by patients treated with Klonopin at multiple doses during clinical trials. All reported events are included except those already listed in Table 3 or elsewhere in labeling, those events for which a drug cause was remote, those event terms which were so general as to be uninformative, and events reported only once and which did not have a substantial probability of being acutely life-threatening. It is important to emphasize that, although the events occurred during treatment with Klonopin, they were not necessarily caused by it.

Events are further categorized by body system and listed in order of decreasing frequency. These adverse events were reported infrequently, which is defined as occurring in 1/100 to 1/1000 patients.

Body as a Whole: weight increase, accident, weight decrease, wound, edema, fever, shivering, abrasions, ankle edema, edema foot, edema periorbital, injury, malaise, pain, cellulitis, inflammation localized

Cardiovascular Disorders: chest pain, hypotension postural

Central and Peripheral Nervous System Disorders: migraine, paresthesia, drunkenness, feeling of enuresis, paresis, tremor, burning skin, falling, head fullness, hoarseness, hyperactivity, hypoesthesia, tongue thick, twitching

Gastrointestinal System Disorders: abdominal discomfort, gastrointestinal inflammation, stomach upset, toothache, flatulence, pyrosis, saliva increased, tooth disorder, bowel movements frequent, pain pelvic, dyspepsia, hemorrhoids

Hearing and Vestibular Disorders: vertigo, otitis, earache, motion sickness

Heart Rate and Rhythm Disorders: palpitation

Metabolic and Nutritional Disorders: thirst, gout

Musculoskeletal System Disorders: back pain, fracture traumatic, sprains and strains, pain leg, pain nape, cramps muscle, cramps leg, pain ankle, pain shoulder, tendinitis, arthralgia, hypertonia, lumbago, pain feet, pain jaw, pain knee, swelling knee

Platelet, Bleeding and Clotting Disorders: bleeding dermal

Psychiatric Disorders: insomnia, organic disinhibition, anxiety, depersonalization, dreaming excessive, libido loss, appetite increased, libido increased, reactions decreased, aggressive reaction, apathy, attention lack, excitement, feeling mad, hunger abnormal, illusion, nightmares, sleep disorder, suicide ideation, yawning

Reproductive Disorders, Female: breast pain, menstrual irregularity

Reproductive Disorders, Male: ejaculation decreased

Resistance Mechanism Disorders: infection mycotic, infection viral, infection streptococcal, herpes simplex infection, infectious mononucleosis, moniliasis

Respiratory System Disorders: sneezing excessive, asthmatic attack, dyspnea, nosebleed, pneumonia, pleurisy

Skin and Appendages Disorders: acne flare, alopecia, xeroderma, dermatitis contact, flushing, pruritus, pustular reaction, skin burns, skin disorder

Special Senses Other, Disorders: taste loss

Urinary System Disorders: dysuria, cystitis, polyuria, urinary incontinence, bladder dysfunction, urinary retention, urinary tract bleeding, urine discoloration

Vascular (Extracardiac) Disorders: thrombophlebitis leg

Vision Disorders: eye irritation, visual disturbance, diplopia, eye twitching, styes, visual field defect, xerophthalmia

DRUG ABUSE AND DEPENDENCE

Controlled Substance Class

Clonazepam is a Schedule IV controlled substance.

Physical and Psychological Dependence

Withdrawal symptoms, similar in character to those noted with barbiturates and alcohol (eg, convulsions, psychosis, hallucinations, behavioral disorder, tremor, abdominal and muscle cramps) have occurred following abrupt discontinuance of clonazepam. The more severe withdrawal symptoms have usually been limited to those patients who received excessive doses over an extended period of time. Generally milder withdrawal symptoms (eg, dysphoria and insomnia) have been reported following abrupt discontinuance of benzodiazepines taken continuously at therapeutic levels for several months. Consequently, after extended therapy, abrupt discontinuation should generally be avoided and a gradual dosage tapering schedule followed (see DOSAGE AND ADMINISTRATION). Addiction-prone individuals (such as drug addicts or alcoholics) should be under careful surveillance when receiving clonazepam or other psychotropic agents because of the predisposition of such patients to habituation and dependence.

Following the short-term treatment of patients with panic disorder in Studies 1 and 2 (see CLINICAL PHARMACOLOGY: Clinical Trials), patients were gradually withdrawn during a 7-week downward-titration (discontinuance) period. Overall, the discontinuance period was associated with good tolerability and a very modest clinical deterioration, without evidence of a significant rebound phenomenon. However, there are not sufficient data from adequate and well-controlled long-term clonazepam studies in patients with panic disorder to accurately estimate the risks of withdrawal symptoms and dependence that may be associated with such use.

OVERDOSAGE

Human Experience

Symptoms of clonazepam overdosage, like those produced by other CNS depressants, include somnolence, confusion, coma and diminished reflexes.

Overdose Management

Treatment includes monitoring of respiration, pulse and blood pressure, general supportive measures and immediate gastric lavage. Intravenous fluids should be administered and an adequate airway maintained. Hypotension may be combated by the use of levarterenol or metaraminol. Dialysis is of no known value.

Flumazenil, a specific benzodiazepine-receptor antagonist, is indicated for the complete or partial reversal of the sedative effects of benzodiazepines and may be used in situations when an overdose with a benzodiazepine is known or suspected. Prior to the administration of flumazenil, necessary measures should be instituted to secure airway, ventilation and intravenous access. Flumazenil is intended as an adjunct to, not as a substitute for, proper management of benzodiazepine overdose. Patients treated with flumazenil should be monitored for resedation, respiratory depression and other residual benzodiazepine effects for an appropriate period after treatment. The prescriber should be aware of a risk of seizure in association with flumazenil treatment, particularly in long-term benzodiazepine users and in cyclic antidepressant overdose. The complete flumazenil package insert, including CONTRAINDICATIONS, WARNINGS and PRECAUTIONS, should be consulted prior to use.

Flumazenil is not indicated in patients with epilepsy who have been treated with benzodiazepines. Antagonism of the benzodiazepine effect in such patients may provoke seizures.

Serious sequelae are rare unless other drugs or alcohol have been taken concomitantly.

DOSAGE AND ADMINISTRATION

Clonazepam is available as a tablet or an orally disintegrating tablet (wafer). The tablets should be administered with water by swallowing the tablet whole. The orally disintegrating tablet should be administered as follows: After opening the pouch, peel back the foil on the blister. Do not push tablet through foil. Immediately upon opening the blister, using dry hands, remove the tablet and place it in the mouth. Tablet disintegration occurs rapidly in saliva so it can be easily swallowed with or without water.

Seizure Disorders

Adults

The initial dose for adults with seizure disorders should not exceed 1.5 mg/day divided into three doses. Dosage may be increased in increments of 0.5 to 1 mg every 3 days until seizures are adequately controlled or until side effects preclude any further increase. Maintenance dosage must be individualized for each patient depending upon response. Maximum recommended daily dose is 20 mg.

The use of multiple anticonvulsants may result in an increase of depressant adverse effects. This should be considered before adding Klonopin to an existing anticonvulsant regimen.

Pediatric Patients

Klonopin is administered orally. In order to minimize drowsiness, the initial dose for infants and children (up to 10 years of age or 30 kg of body weight) should be between 0.01 and 0.03 mg/kg/day but not to exceed 0.05 mg/kg/day given in two or three divided doses. Dosage should be increased by no more than 0.25 to 0.5 mg every third day until a daily maintenance dose of 0.1 to 0.2 mg/kg of body weight has been reached, unless seizures are controlled or side effects preclude further increase. Whenever possible, the daily dose should be divided into three equal doses. If doses are not equally divided, the largest dose should be given before retiring.

Geriatric Patients

There is no clinical trial experience with Klonopin in seizure disorder patients 65 years of age and older. In general, elderly patients should be started on low doses of Klonopin and observed closely (see PRECAUTIONS: Geriatric Use).

Panic Disorder

Adults

The initial dose for adults with panic disorder is 0.25 mg bid. An increase to the target dose for most patients of 1 mg/day may be made after 3 days. The recommended dose of 1 mg/day is based on the results from a fixed dose study in which the optimal effect was seen at 1 mg/day. Higher doses of 2, 3 and 4 mg/day in that study were less effective than the 1 mg/day dose and were associated with more adverse effects. Nevertheless, it is possible that some individual patients may benefit from doses of up to a maximum dose of 4 mg/day, and in those instances, the dose may be increased in increments of 0.125 to 0.25 mg bid every 3 days until panic disorder is controlled or until side effects make further increases undesired. To reduce the inconvenience of somnolence, administration of one dose at bedtime may be desirable.

Treatment should be discontinued gradually, with a decrease of 0.125 mg bid every 3 days, until the drug is completely withdrawn.

There is no body of evidence available to answer the question of how long the patient treated with clonazepam should remain on it. Therefore, the physician who elects to use Klonopin for extended periods should periodically reevaluate the long-term usefulness of the drug for the individual patient.

Pediatric Patients

There is no clinical trial experience with Klonopin in panic disorder patients under 18 years of age.

Geriatric Patients

There is no clinical trial experience with Klonopin in panic disorder patients 65 years of age and older. In general, elderly patients should be started on low doses of Klonopin and observed closely (see PRECAUTIONS: Geriatric Use).

HOW SUPPLIED

Klonopin tablets are available as scored tablets with a K-shaped perforation—0.5 mg, orange (NDC 0004-0068-01); and unscored tablets with a K-shaped perforation—1 mg, blue (NDC 0004-0058-01); 2 mg, white (NDC 0004-0098-01)—bottles of 100.

Imprint on tablets:

0.5 mg | — | 1/2 KLONOPIN (front) ROCHE (scored side)
1 mg | — | 1 KLONOPIN (front) ROCHE (reverse side)
2 mg | — | 2 KLONOPIN (front) ROCHE (reverse side)

Klonopin Wafers (clonazepam orally disintegrating tablets) are white, round and debossed with the tablet strength expressed as a fraction or whole number (1/8, 1/4, 1/2, 1, or 2). The tablets are available in blister packages of 60 (10 pouches/carton) as follows:

0.125 mg | debossed 1/8, (NDC 0004-0279-22)
0.25 mg | debossed 1/4, (NDC 0004-0280-22)
0.5 mg | debossed 1/2, (NDC 0004-0281-22)
1 mg | debossed 1, (NDC 0004-0282-22)
2 mg | debossed 2, (NDC 0004-0283-22)

STORAGE AND HANDLING

Store at 25°C (77°F); excursions permitted to 15° to 30°C (59° to 86°F).

PI Revised: August 2010

Distributed by:

Genentech USA, Inc.
A Member of the Roche Group
1 DNA Way
South San Francisco, CA 94080-4990

KNTW_54023_PI_062010 K

© 2010 Genentech, Inc. All rights reserved.

Medication Guide

KLONOPIN® (KLON-oh-pin)
(clonazepam)
Tablets and Wafers
CIV

Read this Medication Guide before you start taking KLONOPIN and each time you get a refill. There may be new information. This information does not take the place of talking to your healthcare provider about your medical condition or treatment.

KLONOPIN can cause serious side effects. Because stopping KLONOPIN suddenly can also cause serious problems, do not stop taking KLONOPIN without talking to your healthcare provider first.

What is the most important information I should know about KLONOPIN?

Do not stop taking KLONOPIN without first talking to your healthcare provider. Stopping KLONOPIN suddenly can cause serious problems.

KLONOPIN can cause serious side effects, including:

1. KLONOPIN can slow your thinking and motor skills

- Do not drive, operate heavy machinery, or do other dangerous activities until you know how KLONOPIN affects you.
- Do not drink alcohol or take other drugs that may make you sleepy or dizzy while taking KLONOPIN until you talk to your healthcare provider. When taken with alcohol or drugs that cause sleepiness or dizziness, KLONOPIN may make your sleepiness or dizziness worse.

2. Like other antiepileptic drugs, KLONOPIN may cause suicidal thoughts or actions in a very small number of people, about 1 in 500.
Call a healthcare provider right away if you have any of these symptoms, especially if they are new, worse, or worry you:

- thoughts about suicide or dying
- attempt to commit suicide
- new or worse depression
- new or worse anxiety
- feeling agitated or restless
- panic attacks
- trouble sleeping (insomnia)
- new or worse irritability
- acting aggressive, being angry, or violent
- acting on dangerous impulses
- an extreme increase in activity and talking (mania)
- other unusual changes in behavior or mood
  How can I watch for early symptoms of suicidal thoughts and actions?
  - Pay attention to any changes, especially sudden changes, in mood, behaviors, thoughts, or feelings.
  - Keep all follow-up visits with your healthcare provider as scheduled.
    Call your healthcare provider between visits as needed, especially if you are worried about symptoms.
    Suicidal thoughts or actions can be caused by things other than medicines. If you have suicidal thoughts or actions, your healthcare provider may check for other causes.
    Do not stop KLONOPIN without first talking to a healthcare provider.
    Stopping KLONOPIN suddenly can cause serious problems. Stopping KLONOPIN suddenly can cause seizures that will not stop (status epilepticus).

3. KLONOPIN may harm your unborn or developing baby.

- If you take KLONOPIN during pregnancy, your baby is at risk for serious birth defects. These defects can happen as early as in the first month of pregnancy, even before you know you are pregnant. Birth defects may occur even in children born to women who are not taking any medicines and do not have other risk factors.
- Children born to mothers receiving benzodiazepine medications (including KLONOPIN) late in pregnancy may be at some risk of experiencing breathing problems, feeding problems, hypothermia, and withdrawal symptoms.
- Tell your healthcare provider right away if you become pregnant while taking KLONOPIN. You and your healthcare provider should decide if you will take KLONOPIN while you are pregnant.
- If you become pregnant while taking KLONOPIN, talk to your healthcare provider about registering with the North American Antiepileptic Drug Pregnancy Registry. You can register by calling 1-888-233-2334. The purpose of this registry is to collect information about the safety of antiepileptic drugs during pregnancy.
- KLONOPIN can pass into breast milk. Talk to your healthcare provider about the best way to feed your baby if you take KLONOPIN. You and your healthcare provider should decide if you will take KLONOPIN or breast feed. You should not do both.

4. KLONOPIN can cause abuse and dependence.

- Do not stop taking KLONOPIN all of a sudden. Stopping KLONOPIN suddenly can cause seizures that do not stop, hearing or seeing things that are not there (hallucinations), shaking, and stomach and muscle cramps.
  - Talk to your doctor about slowly stopping KLONOPIN to avoid getting sick with withdrawal symptoms.
  - Physical dependence is not the same as drug addiction. Your healthcare provider can tell you more about the differences between physical dependence and drug addiction.

KLONOPIN is a federally controlled substance (C-IV) because it can be abused or lead to dependence. Keep KLONOPIN in a safe place to prevent misuse and abuse. Selling or giving away KLONOPIN may harm others, and is against the law. Tell your doctor if you have ever abused or been dependent on alcohol, prescription medicines or street drugs.

What is KLONOPIN?

KLONOPIN is a prescription medicine used alone or with other medicines to treat:

- certain types of seizure disorders (epilepsy) in adults and children
- panic disorder with or without fear of open spaces (agoraphobia) in adults

It is not known if KLONOPIN is safe or effective in treating panic disorder in children younger than 18 years old.

Who should not take KLONOPIN?

Do not take KLONOPIN if you:

- are allergic to benzodiazepines
- have significant liver disease
- have an eye disease called acute narrow angle glaucoma

Ask your healthcare provider if you are not sure if you have any of the problems listed above.

What should I tell my healthcare provider before taking KLONOPIN?

Before you take KLONOPIN, tell your healthcare provider if you:

- have liver or kidney problems
- have lung problems (respiratory disease)
- have or have had depression, mood problems, or suicidal thoughts or behavior
- have any other medical conditions

Tell your healthcare provider about all the medicines you take, including prescription and non-prescription medicines, vitamins, and herbal supplements. Taking KLONOPIN with certain other medicines can cause side effects or affect how well they work. Do not start or stop other medicines without talking to your healthcare provider.

Know the medicines you take. Keep a list of them and show it to your healthcare provider and pharmacist when you get a new medicine.

How should I take KLONOPIN?

- Take KLONOPIN exactly as your healthcare provider tells you. KLONOPIN is available as a tablet or as an orally disintegrating tablet (wafer).
- Do not stop taking KLONOPIN without first talking to your healthcare provider. Stopping KLONOPIN suddenly can cause serious problems.
- KLONOPIN tablets should be taken with water and swallowed whole.
- KLONOPIN wafers can be taken with or without water.
  - Do not open the pouch until you are ready to take KLONOPIN.
  - After opening the pouch, peel back the foil on the blister pack.
  - Do not push the wafer through the foil.
  - After opening the blister pack, with dry hands, take the wafer and place it in your mouth.
  - The wafer will melt quickly.
- If you take too much KLONOPIN, call your healthcare provider or local Poison Control Center right away.

What should I avoid while taking KLONOPIN?

- KLONOPIN can slow your thinking and motor skills. Do not drive, operate heavy machinery, or do other dangerous activities until you know how KLONOPIN affects you.
- Do not drink alcohol or take other drugs that may make you sleepy or dizzy while taking KLONOPIN until you talk to your healthcare provider. When taken with alcohol or drugs that cause sleepiness or dizziness, KLONOPIN may make your sleepiness or dizziness worse.

What are the possible side effects of KLONOPIN?

See " What is the most important information I should know about KLONOPIN?"

KLONOPIN can also make your seizures happen more often or make them worse. Call your healthcare provider right away if your seizures get worse while taking KLONOPIN.

The most common side effects of KLONOPIN include:

- Drowsiness
- Problems with walking and coordination
- Dizziness
- Depression
- Fatigue
- Problems with memory

These are not all the possible side effects of KLONOPIN. For more information, ask your healthcare provider or pharmacist.

Tell your healthcare provider if you have any side effect that bothers you or that does not go away.

Call your doctor for medical advice about side effects. You may report side effects to FDA at 1-800-FDA-1088 or Genentech at 1-888-835-2555.

How should I store KLONOPIN?

- Store KLONOPIN between 59°F to 86°F (15°C to 30°C)

Keep KLONOPIN and all medicines out of the reach of children.

General Information about KLONOPIN

Medicines are sometimes prescribed for purposes other than those listed in a Medication Guide. Do not use KLONOPIN for a condition for which it was not prescribed. Do not give KLONOPIN to other people, even if they have the same symptoms that you have. It may harm them.

This Medication Guide summarizes the most important information about KLONOPIN. If you would like more information, talk with your healthcare provider. You can ask your pharmacist or healthcare provider for information about KLONOPIN that is written for health professionals.

For more information, go to www.gene.com/gene/products/information/klonopin or call 1-888-835-2555.

What are the ingredients in KLONOPIN?

Active ingredient: clonazepam

Inactive ingredients:

- Tablets:
  - 0.5 mg tablets contain lactose, magnesium stearate, microcrystalline cellulose, corn starch, FDandC Yellow No. 6 Lake
  - 1 mg tablets contain lactose, magnesium stearate, microcrystalline cellulose, corn starch, FDandC Blue No. 1 Lake and FDandC Blue No. 2 Lake
  - 2 mg tablets contain lactose, magnesium stearate, microcrystalline cellulose, corn starch
- Wafers: gelatin, mannitol, methylparaben sodium, propylparaben sodium and xanthan gum

MG Issued: August 2010

This Medication Guide has been approved by the U.S. Food and Drug Administration.

Disbributed by:

Genentech USA, Inc.
A Member of the Roche Group
1 DNA Way
South San Francisco, CA 94080-4990

KNTW_54023_MG_062010_K

© 2010 Genentech, Inc. All rights reserved.

For additional copies of this Medication Guide, please call 1-877-436-3683 or visit www.gene.com/gene/products/information/klonopin.

ATTENTION PHARMACIST: Dispense the accompanying
Medication Guide to each patient. For additional
Medication Guides call 1-877-436-3683 or visit
www.gene.com/gene/products/information/klonopin.